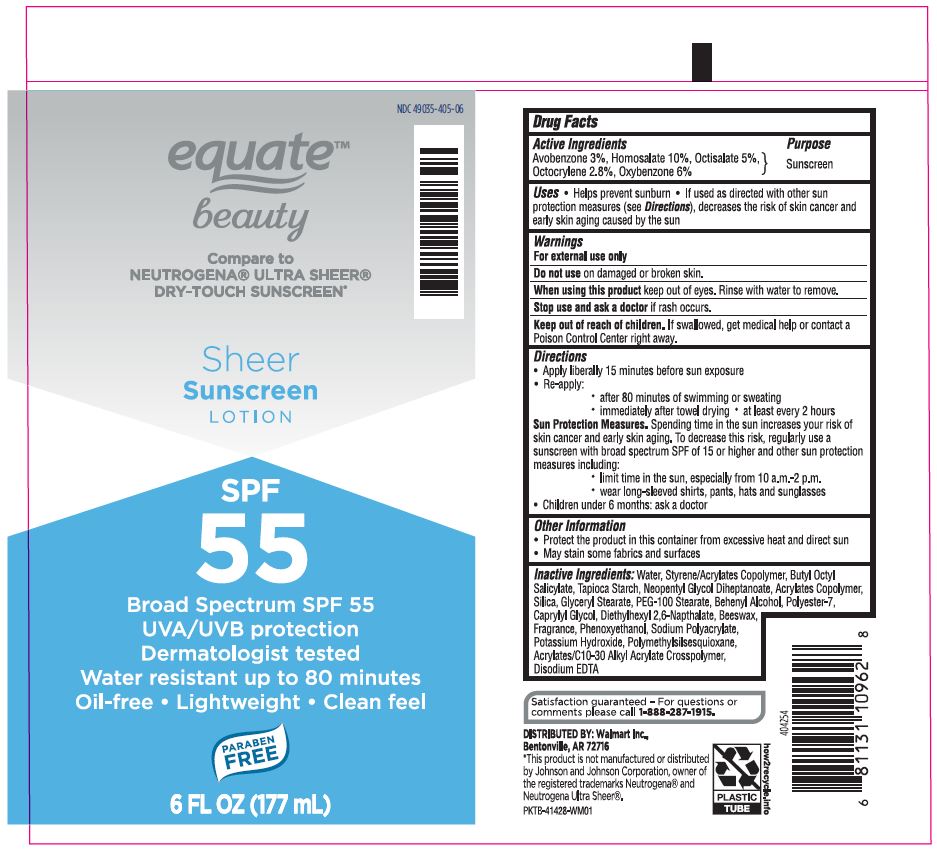 DRUG LABEL: Avobenzone, Homosalate, Octisalate, Octocrylene, Oxybenzone
NDC: 49035-405 | Form: LOTION
Manufacturer: Wal-Mart Stores Inc.
Category: otc | Type: HUMAN OTC DRUG LABEL
Date: 20190626

ACTIVE INGREDIENTS: HOMOSALATE 10 g/100 g; OCTOCRYLENE 3 g/100 g; OXYBENZONE 6 g/100 g; AVOBENZONE 3 g/100 g; OCTISALATE 5 g/100 g
INACTIVE INGREDIENTS: BUTYL OCTYL PHTHALATE; CAPRYLYL GLYCOL; BUTYL ACRYLATE/METHYL METHACRYLATE/METHACRYLIC ACID COPOLYMER (18000 MW); NEOPENTYL GLYCOL DIHEPTANOATE; EDETATE DISODIUM; HYDRATED SILICA; DOCOSANOL; GLYCERYL STEARATE/PEG-100 STEARATE; POLYESTER-7; DIETHYLHEXYL 2,6-NAPHTHALATE; PHENOXYETHANOL; YELLOW WAX; POLYMETHYLSILSESQUIOXANE (4.5 MICRONS); POTASSIUM HYDROXIDE; SODIUM POLYACRYLATE (2500000 MW); STARCH, TAPIOCA; WATER

Private Label Equate Beauty Ultra Sheer Sunscreen SPF 55

Active Ingredients

Avobenzone 3%, Homosalate 10%, Octisalate 5%, Octocyrlene 2.8% Oxybenzone 6%

Purpose

Sunscreen

Uses

• Helps prevent sunburn • If used as directed with other sun protection measure (see Directions), decreases the risk of skin cancer and early skin aging caused by the sun.

Warnings

For external use only

Do not use on damaged or broken skin.

When using this product keep out of eyes. Rinse with water to remove.

Stop use and ask a doctor if rash occurs.

Keep out of reach of children. If swallowed, get medical help or contact a Poison Control Center right away.

Directions

Apply liberally 15 minutes before sun exposure.

• after 80 minutes of swimming or sweating

• immediately after towel drying

Sun Protection Measures. Spending time in the sun increases your risk of skin cancer and early skin aging. To decrease this risk, regularly use a sunscreen with broad spectrum of SPF of 15 or higher and other sun protection measures including:

• limit time in the sun, especially 10a.m.-2a.m.

• wear long-sleeved shirts, pants, hats and sunglasses

•Children under 6 months: ask a doctor

Other Information

• Protect the product in this container from excessive heat and direct sun

• May stain some fabrics and surfaces

Inactive Ingredients

Water, Acrylates Copolymer, Styrene/Acrylates Copolymer, Butyl Octyl Salicylate, Tapioca Starch, Neopentyl Glycol Diheptanoate, Silica, Glyceryl Stearate, PEG-100 Stearate, Behenyl Alcohol, Caprylyl Glycol, Diethylhexyl 2,6-Naptnalate, Polyester-7, Beeswax, Fragrance, Phenoxyethanol, Potassium Hydroxide, Acrylates/C10-30 Alkyl Acrylate Crosspolymer, Sodium Polyacrylate, Polymethylsilsesquioxane, Disodium EDTA

Questions

Satisfaction guaranteed - For questions or comments please call 1-888-287-1915.

DISTRIBUTED BY: Walmart Inc.,

Bentonville, AR 72716

*This product is not manufactured or distributed by Johnson and Johnson Corporation,m owner of the registered trademarks Neutrogena® and Neutrogena Ultra Sheer®.

PKTB-41429-WM01

Principal Display Panel

EquateTM beauty

Compare to NEUTROGENA® ULTRA SHEER®

DRY-TOUCH SUNSCREEN*

Sheer

Sunscreen

LOTION

SPF

55

Broad Spectrum SPF 55

UVA/UVB protection

Dermatologist tested

Water resistant up to 80 minutes

Oil-free • Lightweight • Clean feel

PARABEN FREE

6 FL OZ (177mL)